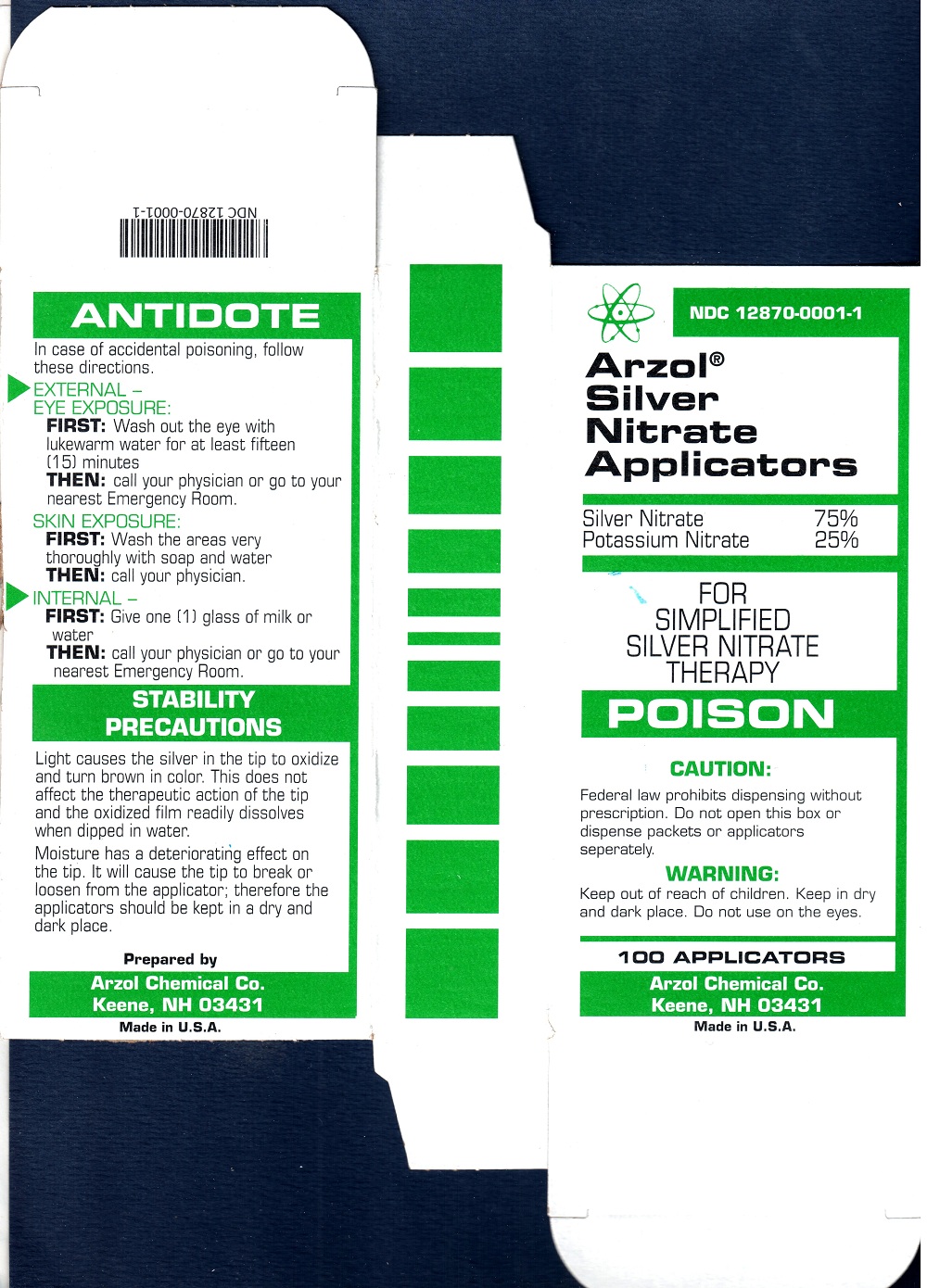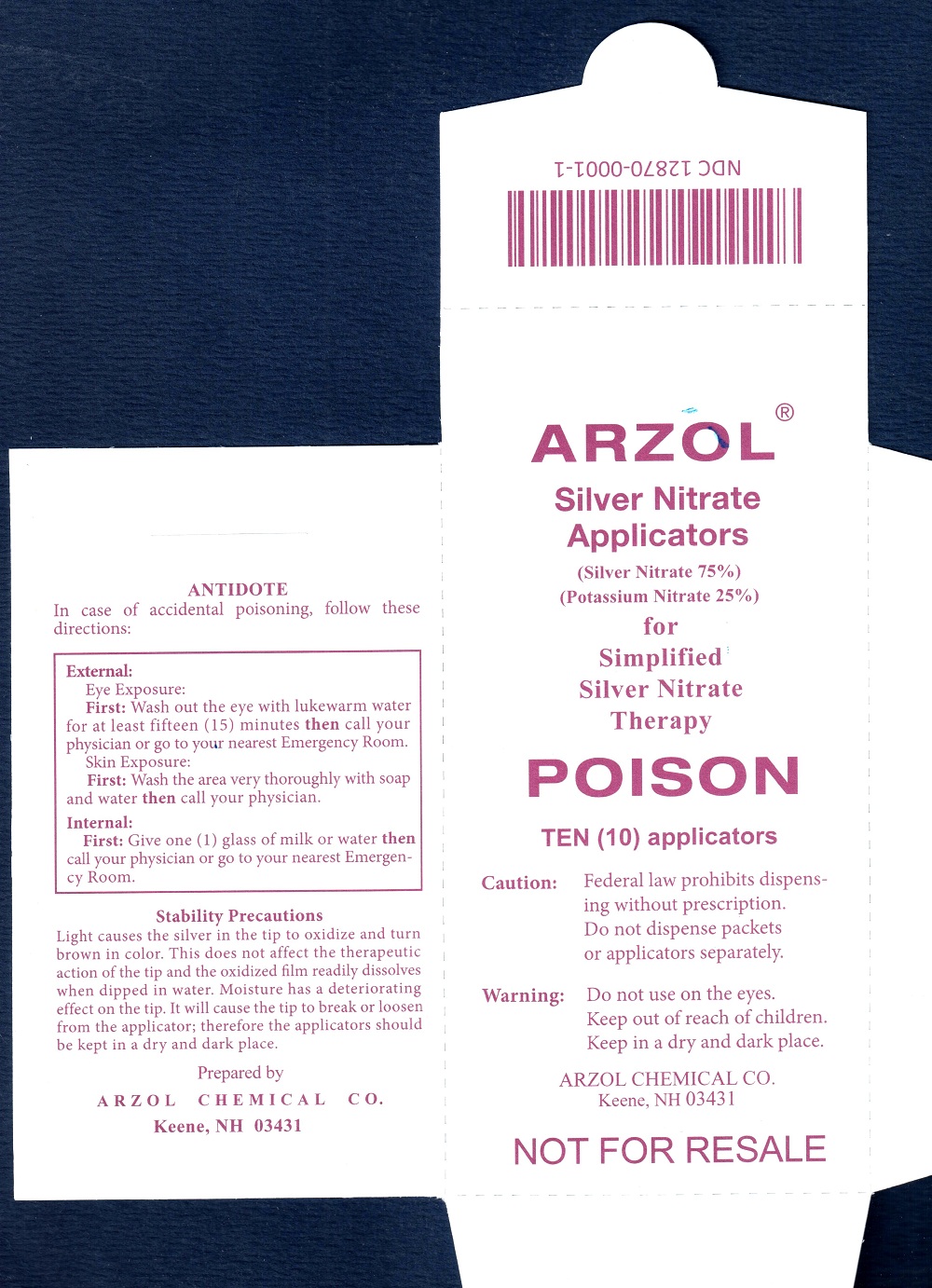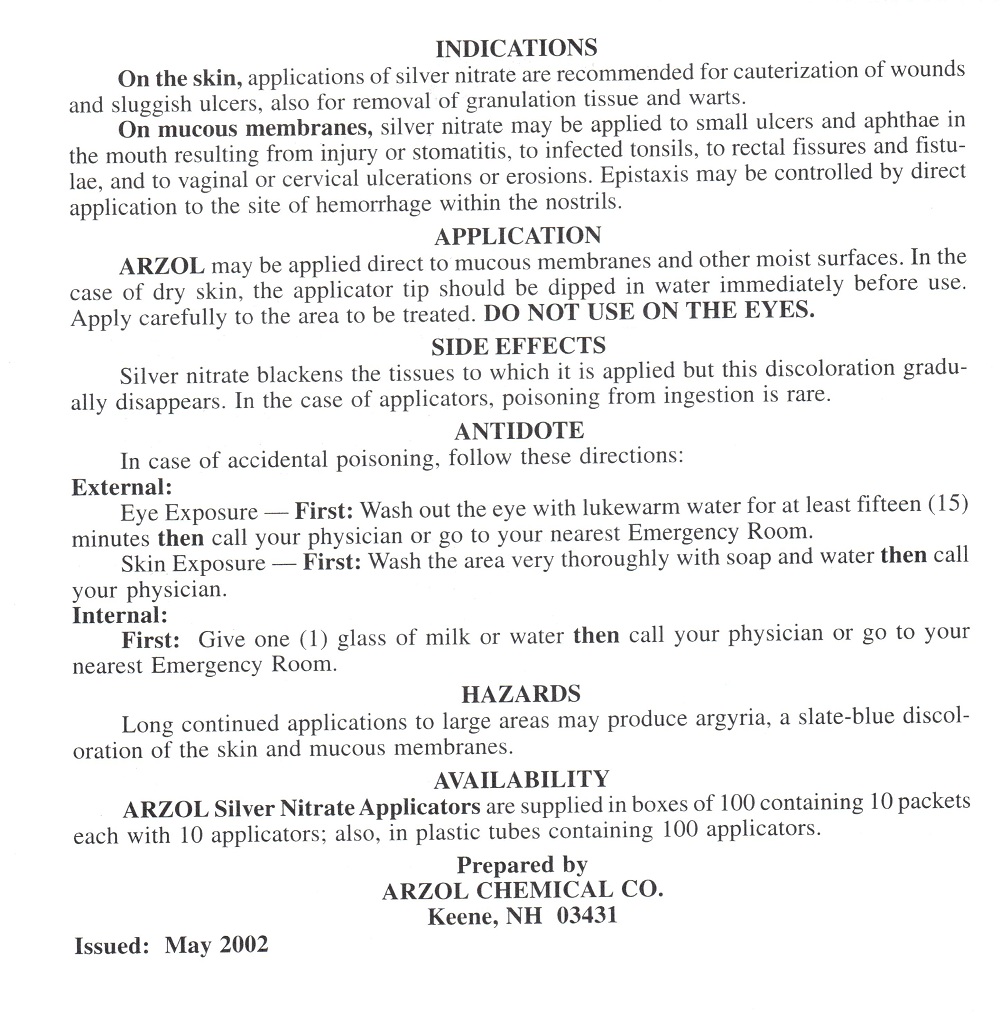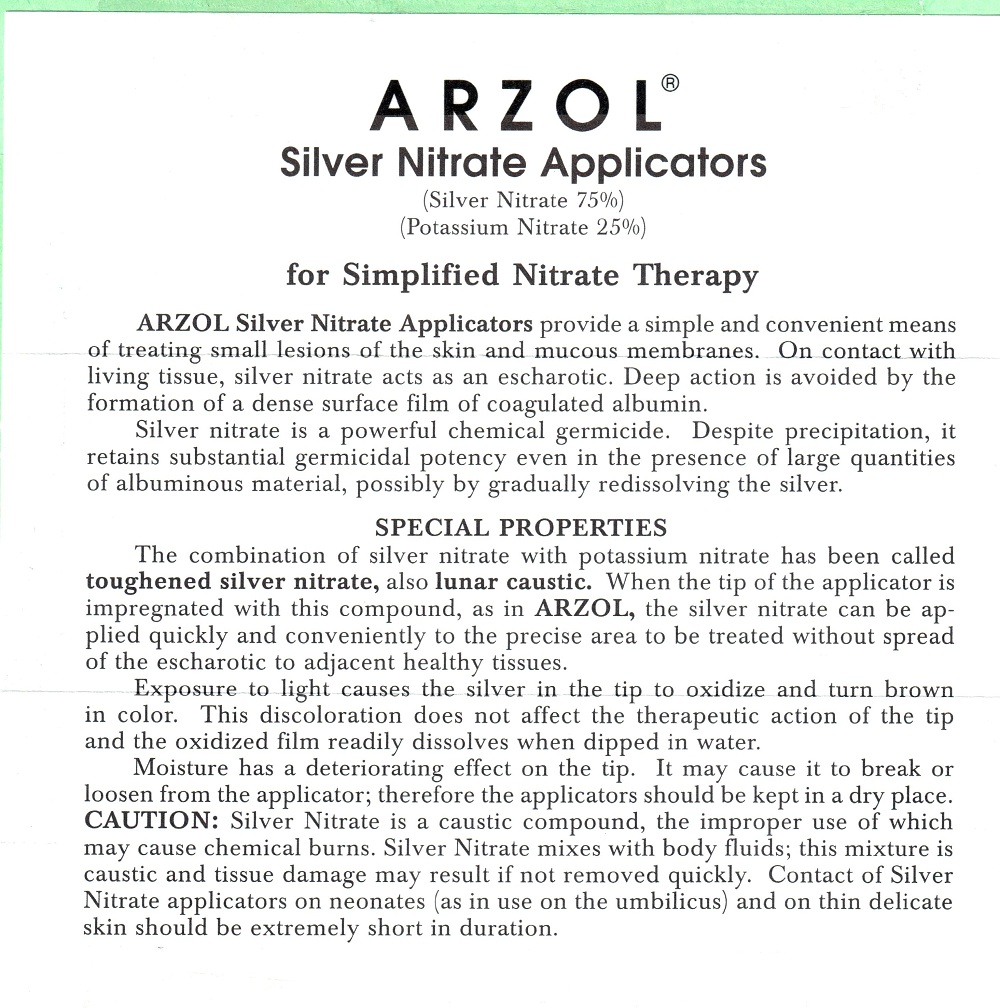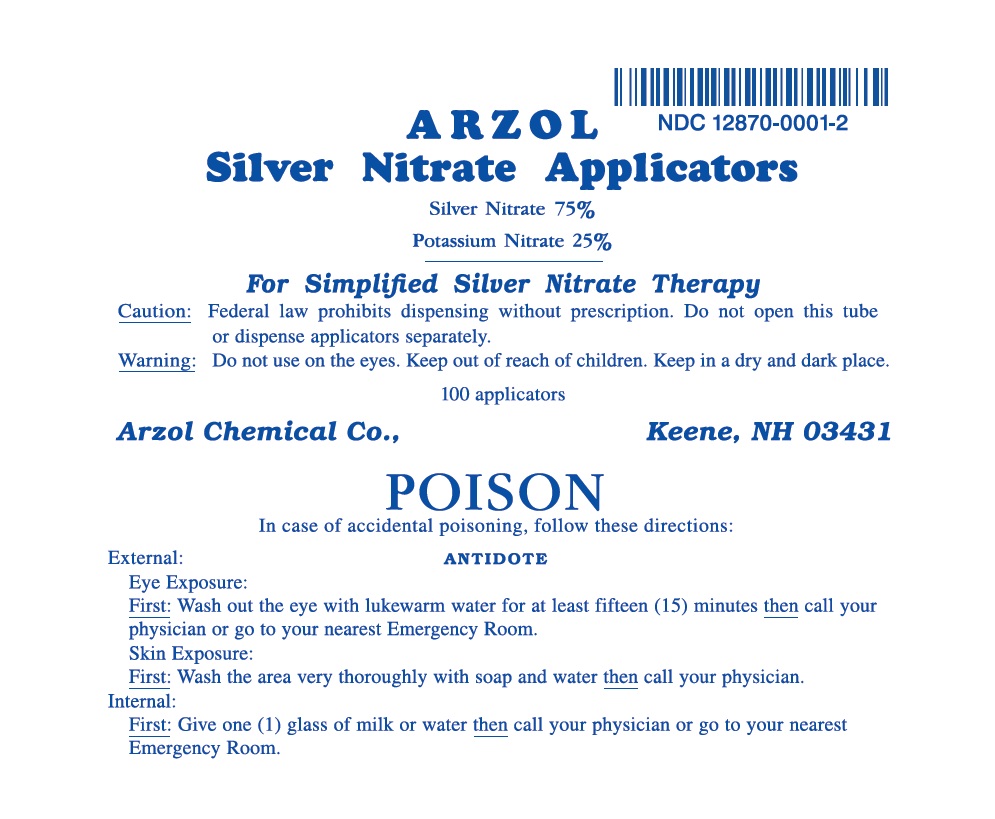 DRUG LABEL: Silver Nitrate Applicators
NDC: 12870-0001 | Form: STICK
Manufacturer: Arzol Chemical Company
Category: prescription | Type: HUMAN PRESCRIPTION DRUG LABEL
Date: 20251029

ACTIVE INGREDIENTS: POTASSIUM NITRATE 25 mg/100 mg; SILVER NITRATE 75 mg/100 mg

INSTRUCTIONS FOR USE

STATEMENT OF IDENTITY

ARZOL® Silver Nitrate Applicators

DOSAGE FORMS AND STRENGTHS

Silver Nitrate 75%

Potassium Nitrate 25%

DESCRIPTION

for Simplified Silver Nitrate Therapy

ARZOL Silver Nitrate Applicators provide a simple and convenient means of treating small lesions of the skin and mucous membranes. On contact with living tissue, silver nitrate acts as an escharotic. Deep action is avoided by the formation of a dense surface film of coagulated albumin.

Silver nitrate is a powerful chemical germicide. Despite precipitation, it retains substantial germicidal potency even in the presence of large quantities of albuminous material, possibly by gradually redissolving the silver.

SPECIAL PROPERTIES

The combination of silver nitrate with potassium nitrate has been called toughened silver nitrate, also lunar caustic. When the tip of the applicator is impregnated with this compound, as in ARZOL, the silver nitrate can be applied quickly and conveniently to the precise area to be treated without spread of the escharotic to adjacent healthy tissues.

Exposure to light causes the silver in the tip to oxidize and turn brown in color. This discoloration does not affect the therapeutic action of the tip and the oxidized film readily dissolves when dipped in water.

Moisture has a deteriorating effect on the tip. It may cause it to break or loosen from the applicator; therefore the applicators should be kept in a dry place.

CAUTION: Silver Nitrate is a caustic compound, the improper use of which may cause chemical burns. Silver Nitrate mixes with body fluids; this mixture is caustic and tissue damage may result if not removed quickly. Contact of Silver Nitrate applicators on neonates (as in use on the umbilicus) and on thin delicate skin should be extremely short in duration.

INDICATIONS

On the skin, applications of silver nitrate are recommended for cauterization of wounds and sluggish ulcers, also for removal of granulation tissue and warts.

On mucous membranes, silver nitrate may be applied to small ulcers and aphthae in the mouth resulting from injury or stomatitis, to infected tonsils, to rectal fissures and fistulae, and to vaginal or cervical ulcerations or erosions. Epistaxis may be controlled by direct application to the site of hemorrhage within the nostrils.

APPLICATION

ARZOL may be applied direct to mucous membranes and other moist surfaces. In the case of dry skin, the applicator tip should be dipped in water immediately before use. Apply carefully to the area to be treated. DO NOT USE ON THE EYES.

SIDE EFFECTS

Silver nitrate blackens the tissues to which it is applied but this discoloration gradually disappears. In the case of applicators, poisoning from ingestion is rare.

ANTIDOTE

In case of accidental poisoning, follow these directions:

External:

Eye Exposure -- First: Wash out the eye with lukewarm water for at least fifteen (15) minutes then call your physician or go to your nearest Emergency Room.

Skin Exposure -- First: Wash the area very thoroughly with soap and water then call your physician.

Internal:

First: Give one (1) glass of milk or water then call your physician or go to your nearest Emergency Room.

HAZARDS

Long continued applications to large areas may produce argyria, a slate-blue discoloration of the skin and mucous membranes.

AVAILABILITY

ARZOL Silver Nitrate Applicators are supplied in boxes of 100 containing 10 packets each with 10 applicators; also, in plastic tubes containing 100 applicators.

PACKAGE LABEL

STATEMENT OF IDENTITY

Arzol® Silver Nitrate Applicators

DOSAGE FORMS AND STRENGTHS

Silver Nitrate 75%

Potassium Nitrate 25%

DESCRIPTION

FOR SIMPLIFIED SILVER NITRATE THERAPY

WARNINGS

POISON

WARNINGS

CAUTION:

Federal law prohibits dispensing without prescription. Do not open this box or dispense packets or applicators separately.

WARNING:

Keep out of reach of children. Keep in dry and dark place. Do not use on the eyes.

HOW SUPPLIED

100 APPLICATORS

ANTIDOTE

In case of accidental poisoning, follow these directions.

EXTERNAL -

EYE EXPOSURE:

FIRST: Wash out the eye with lukewarm water for at least fifteen (15) minutes

THEN: call your physician or go to your nearest Emergency Room.

SKIN EXPOSURE:

FIRST: Wash the areas very thoroughly with soap and water

THEN: call your physician.

INTERNAL:

FIRST: Give one (1) glass of milk or water

THEN: call your physician or go to your nearest Emergency Room.

STABILITY PRECAUTIONS

Light causes the silver in the tip to oxidize and turn brown in color. This does not affect the therapeutic action of the tip and the oxidized film readily dissolves when dipped in water.

Moisture has a deteriorating effect on the tip. It will cause the tip to break or loosen from the applicator; therefore the applicators should be kept in a dry and dark place.

PACKAGE LABEL

STATEMENT OF IDENTITY

ARZOL® Silver Nitrate Applicators

DOSAGE FORMS AND STRENGTHS

(Silver Nitrate 75%)

(Potassium Nitrate 25%)

DESCRIPTION

for Simplified Silver Nitrate Therapy

WARNINGS

POISON

HOW SUPPLIED

TEN (10) applicators

WARNINGS

Caution: Federal law prohibits dispensing without prescription. Do not dispense packets or applicators separately.

WARNINGS AND PRECAUTIONS

Warning: Do not use on the eyes. Keep out of reach of children. Keep in a dry and dark place.

WARNINGS

NOT FOR RESALE

ANTIDOTE

In case of accidental poisoning, follow these directions:

External:

Eye Exposure:

First: Wash out the eye with lukewarm water for at least fifteen (15) minutes then call your physician or go to your nearest Emergency Room.

Skin Exposure:

First: Wash the area very thoroughly with soap and water then call your physician.

Internal:

First: Give one (1) glass of milk or water then call your physician or go to your nearest Emergency Room.

Stability Precautions

Light causes the silver in the tip to oxidize and turn brown in color. This does not affect the therapeutic action of the tip and the oxidized film readily dissolves when dipped in water. Moisture has a deteriorating effect on the tip. It will cause the tip to break or loosen from the applicator; therefore the applicators should be kept in a dry and dark place.

PACKAGE LABEL

STATEMENT OF IDENTITY

ARZOL Silver Nitrate Applicators

DOSAGE FORMS AND STRENGTHS

Silver Nitrate 75%

Potassium Nitrate 25%

DESCRIPTION

For Simplified Silver Nitrate Therapy

WARNINGS

Caution: Federal law prohibits dispensing without prescription. Do not open this tube or dispense applicators separately.

WARNINGS AND PRECAUTIONS

Warning: Do not use on the eyes. Keep out of reach of children. Keep in a dry and dark place.

WARNINGS

POISON

OTHER SAFETY INFORMATION

In case of accidental poisoning, follow these directions:

ANTIDOTE

External:

Eye Exposure:

First: Wash out the eye with lukewarm water for at least fifteen (15) minutes then call your physician or go to your nearest Emergency Room.

Skin Exposure:

First: Wash the area very thoroughly with soap and water then call your physician.

Internal:

First: Give one (1) glass of milk or water then call your physician or go to your nearest Emergency Room.